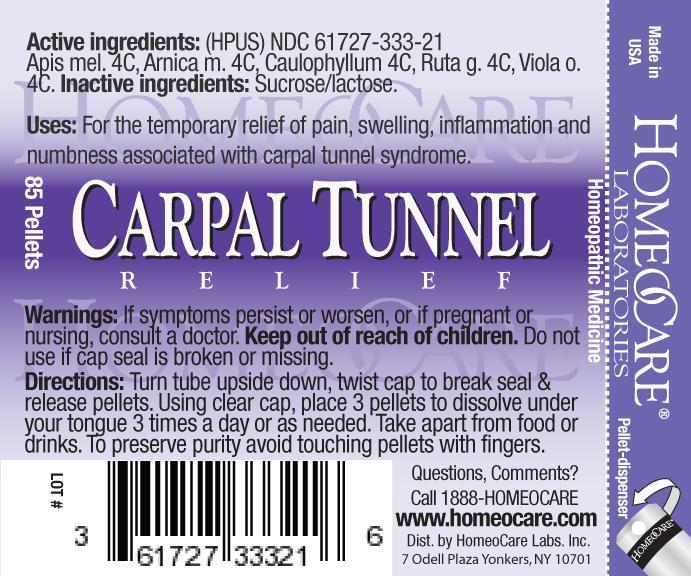 DRUG LABEL: Carpal Tunnel Relief
NDC: 61727-333 | Form: PELLET
Manufacturer: Homeocare Laboratories
Category: homeopathic | Type: HUMAN OTC DRUG LABEL
Date: 20181231

ACTIVE INGREDIENTS: APIS MELLIFERA 4 [hp_C]/4 g; ARNICA MONTANA 4 [hp_C]/4 g; CAULOPHYLLUM ROBUSTUM ROOT 4 [hp_C]/4 g; RUTA GRAVEOLENS FLOWERING TOP 4 [hp_C]/4 g; VIOLA ODORATA 4 [hp_C]/4 g
INACTIVE INGREDIENTS: SUCROSE; LACTOSE

Carpal Tunnel Relief

Active Ingredients:(HPUS)

Apis Mel 4C, Arnica M. 4C, Caulophyllum 4C, Ruta G. 4C, Viola O. 4C.

Purpose:

For the temporary relief of pain, swelling, inflammation and numbness associated with carpal tunnel syndrome.

Keep out of reach of children.

Uses:

For the temporary relief of pain, swelling, inflammation and numbness associated with carpal tunnel syndrome.

Warnings:

If symptoms persist or worsen, or if pregnant or nursing, consult a doctor. Keep out of reach of children. Do not use if cap seal is broken or missing.

Inactive Ingredients:

Sucrose/lactose.

Dosage & Administration:

Turn tube upside down, twist cap to break seal & release pellets. Using clear cap, place 3 pellets to dissolve under your tongue 3 times a day or as needed. Take apart from food or drinks. To preserve purity avoid touching pellets with fingers.